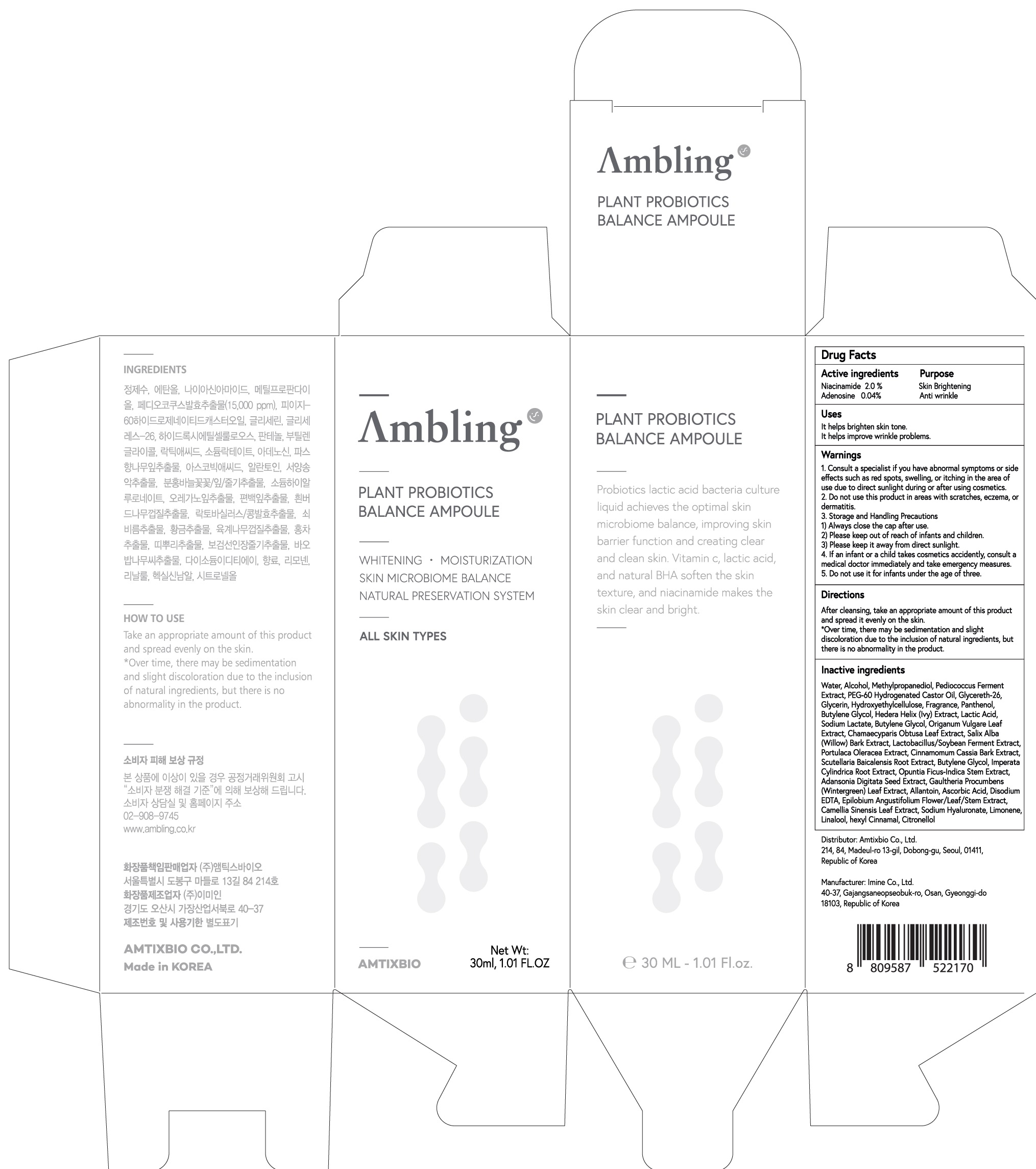 DRUG LABEL: Ambling Plant Probiotics Balance Ampoule
NDC: 73456-010 | Form: LIQUID
Manufacturer: Amtixbio Co., Ltd.
Category: otc | Type: HUMAN OTC DRUG LABEL
Date: 20220216

ACTIVE INGREDIENTS: Niacinamide 0.60 g/30 mL; Adenosine 0.012 g/30 mL
INACTIVE INGREDIENTS: Water; Alcohol

ACTIVE INGREDIENTS

Niacinamide 2.0%, Adenosine 0.04%

INACTIVE INGREDIENTS

Water, Alcohol, Methylpropanediol, Pediococcus Ferment Extract, PEG-60 Hydrogenated Castor Oil, Glycereth-26, Glycerin, Hydroxyethylcellulose, Fragrance, Panthenol, Butylene Glycol, Hedera Helix (Ivy) Extract, Lactic Acid, Sodium Lactate, Butylene Glycol, Origanum Vulgare Leaf Extract, Chamaecyparis Obtusa Leaf Extract, Salix Alba (Willow) Bark Extract, Lactobacillus/Soybean Ferment Extract, Portulaca Oleracea Extract, Cinnamomum Cassia Bark Extract, Scutellaria Baicalensis Root Extract, Butylene Glycol, Imperata Cylindrica Root Extract, Opuntia Ficus-Indica Stem Extract, Adansonia Digitata Seed Extract, Gaultheria Procumbens (Wintergreen) Leaf Extract, Allantoin, Ascorbic Acid, Disodium EDTA, Epilobium Angustifolium Flower/Leaf/Stem Extract, Camellia Sinensis Leaf Extract, Sodium Hyaluronate, Limonene, Linalool, hexyl Cinnamal, Citronellol

PURPOSE

Skin Brightening, Anti wrinkle

WARNINGS

1. Consult a specialist if you have abnormal symptoms or side effects such as red spots, swelling, or itching in the area of use due to direct sunlight during or after using cosmetics.

2. Do not use this product in areas with scratches, eczema, or dermatitis.

3. Storage and Handling Precautions
1) Always close the cap after use.
2) Please keep out of reach of infants and children.
3) Please keep it away from direct sunlight.

4. If an infant or a child takes cosmetics accidently, consult a medical doctor immediately and take emergency measures.

5. Do not use it for infants under the age of three.

KEEP OUT OF REACH OF CHILDREN

If an infant or a child takes cosmetics accidently, consult a medical doctor immediately and take emergency measures.

Uses

It helps brighten skin tone.
It helps improve wrinkle problems.

Directions

After cleansing, take an appropriate amount of this product and spread it evenly on the skin.

*Over time, there may be sedimentation and slight discoloration due to the inclusion of natural ingredients, but there is no abnormality in the product.